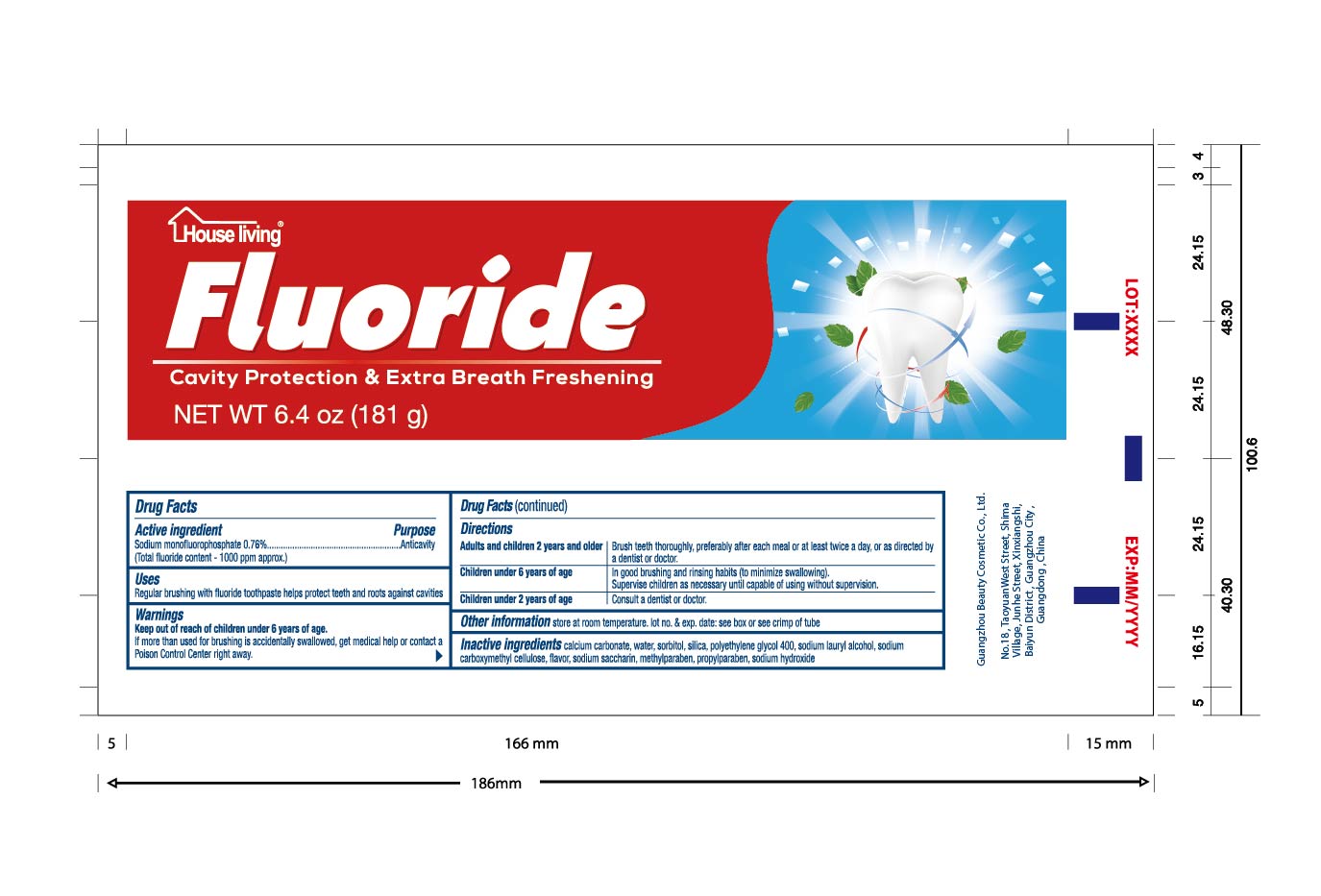 DRUG LABEL: House Living
NDC: 71704-001 | Form: PASTE
Manufacturer: Guangzhou Beauty Cosmetic Co., Ltd
Category: otc | Type: HUMAN OTC DRUG LABEL
Date: 20170908

ACTIVE INGREDIENTS: SODIUM MONOFLUOROPHOSPHATE 0.76 g/100 g
INACTIVE INGREDIENTS: METHYLPARABEN; PROPYLPARABEN; CALCIUM CARBONATE; CARBOXYMETHYLCELLULOSE SODIUM; SILICON DIOXIDE; SACCHARIN SODIUM; WATER; SODIUM LAURYL SULFATE; POLYETHYLENE GLYCOL 400; SORBITOL; SODIUM HYDROXIDE

Active ingredients

SODIUM MONOFLUOROPHOSPHATE 0.76%

Purpose

anticavity

Uses

Regular brushing with fluoride toothpaster helps protect teeth and roots against cavities.

Warnings

Keep out of the reach of children under 6 years of age.if more than used for brushing is accidentally swalowed, get medical help or contact a Poison Control Center right away.

Keep out of reach of children.

Directions

Adults and children 2years of age and older:Brush teeth thoroughly,preferably after each meal or at least twice a day,or as directed by a dentist or a doctor.

Children under 6 years of age ,in good brushing and rinsing habits (to minimize swallowing),

supervise children as necessary until capable of useing without supervision.

Children under 2 years of age:consult a dentist or doctor.

INACTIVE INGREDIENT

Water,Silica ,Calcium Carbonate,Sodium Lauryl Alcohol,Sorbitol,Polyethylene Glycol 400, Sodium Carboxymethylcellulose,Sodium Saccharin,Sodium Hydroxide,Methyl Paraben,Propylparaben,Flavor